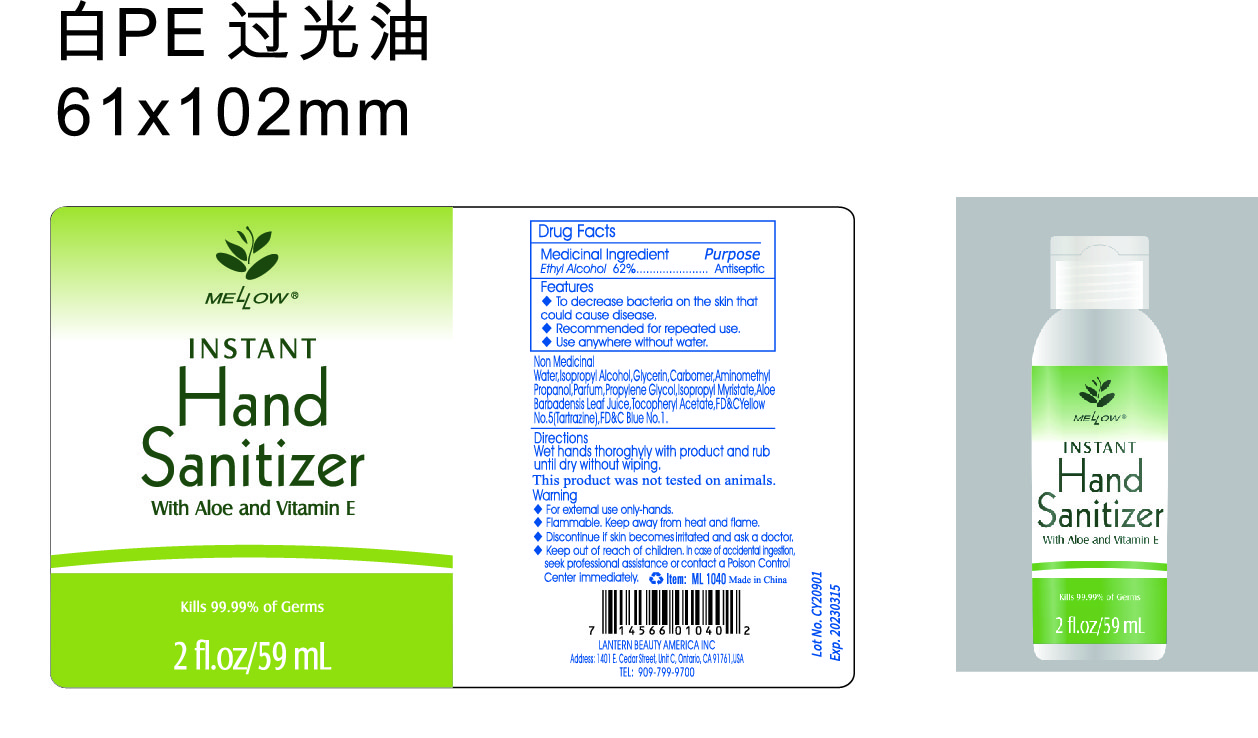 DRUG LABEL: Instant hand sanitizer with aloe and vitamin E
NDC: 54860-142 | Form: LIQUID
Manufacturer: Shenzhen Lantern Science Co.,Ltd
Category: otc | Type: HUMAN OTC DRUG LABEL
Date: 20200410

ACTIVE INGREDIENTS: ALCOHOL 62 g/100 g
INACTIVE INGREDIENTS: ALOE VERA LEAF 0.1 g/100 g; ALOE 0.15 g/100 g; ISOPROPYL MYRISTATE 0.001 g/100 g; FD&C YELLOW NO. 5 0.00006 g/100 g; CARBOMER 940 0.26 g/100 g; WATER 36.307916 g/100 g; ISOPROPYL ALCOHOL 0.5 g/100 g; AMINOMETHYLPROPANOL 0.08 g/100 g; FD&C BLUE NO. 1 0.000024 g/100 g; .ALPHA.-TOCOPHEROL ACETATE 0.001 g/100 g; GLYCERIN 0.5 g/100 g; PROPYLENE GLYCOL 0.1 g/100 g

Instant hand sanitizer with aloe and vitamin E

Medicical Ingredient

Medicical Ingredient Purpose

Ethyl Alcohol 62% Antiseptic

Features

To decrease bacteria on the skin that could cause disease.

DOSAGE AND ADMINISTRATION

Recommended for repeated use.

use anywhere without water.

Warning

WARNINGS AND PRECAUTIONS

For external use only.

Flammable, keep away from heat and flame.

STOP USE

Discontinue if skin becomes irritated and ask a doctor .

Keep out of reach of children. In case of accidental ingestion, seek professional assistance or contact a poson control center immediately.

Non-Medicinal

Alcohol，Aqua(water)，Isopropyl Alcohol，Glycerin，Carbomer，Aminomethyl Propanol，Parfum，Propylene Glycol，ISOPROPYL MYRISTATE，ALOE BARBADENSIS LEAF JUICE，Tocopheryl Acetate，YELLOW 5，BLUE 1

Directions

Wet hands thoroughly with product and rub until dry without wiping

For children under 6, use only under adult supervision.

Not recommended for infants.

When using this product

keep out of eyes. In case of contact with eyes, flush thoroughly with water.

Do not inhale or ingest.

Avoid contact with broken skin.

Other information

Do not store above 105F.

May discolor some fabrics.

Harmful to wood finishes and plastics.